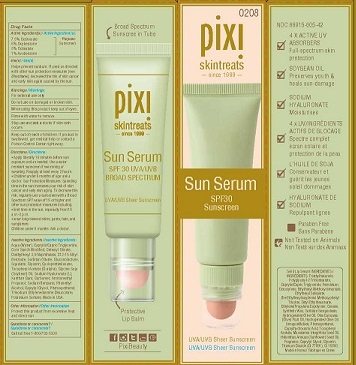 DRUG LABEL: PIXI SUN SERUM SPF 30
NDC: 70686-102 | Form: CREAM
Manufacturer: PIXI, INC
Category: otc | Type: HUMAN OTC DRUG LABEL
Date: 20181108

ACTIVE INGREDIENTS: AVOBENZONE 1 g/100 mL; OCTINOXATE 7.5 g/100 mL; OCTISALATE 5 g/100 mL; OXYBENZONE 6 g/100 mL
INACTIVE INGREDIENTS: WATER; MEDIUM-CHAIN TRIGLYCERIDES; STARCH, CORN; CETEARYL OLIVATE; DIETHYLHEXYL 2,6-NAPHTHALATE; ALKYL (C12-15) BENZOATE; SORBITAN OLIVATE; GLUCONOLACTONE; SQUALANE; GLYCERIN; CYCLOMETHICONE 5; .ALPHA.-TOCOPHEROL ACETATE; SOYBEAN OIL; HYALURONATE SODIUM; XANTHAN GUM; CARBOXYPOLYMETHYLENE; AMINOMETHYLPROPANOL; SODIUM BENZOATE; PHENYLETHYL ALCOHOL; CAPRYLYL GLYCOL; PHENOXYETHANOL; TRISODIUM ETHYLENEDIAMINE DISUCCINATE; POTASSIUM SORBATE

ACTIVE INGREDIENTS

OCTINOXATE (7.5%)

OXYBENZONE (6%)

OCTISALATE (5%)

AVOBENZONE (1%)

PURPOSE

SUNSCREEN

USES

HELPS PREVENT SUNBURN. IF USED AS DIRECTED WITH OTHER SUN PROTECTION MEASURES (SEE DIRECTIONS), DECREASES THE RISK OF SKIN CANCER AND EARLY SKIN AGING CAUSED BY THE SUN.

WARNINGS

FOR EXTERNAL USE ONLY.

DO NOT USE ON DAMAGED OR BROKEN SKIN.

WHEN USING THIS PRODUCT KEEP OUT OF EYES. RINSE WITH WATER TO REMOVE.

STOP USE AND ASK A DOCTOR IF SKIN RASH OCCURS.

KEEP OUT OF REACH OF CHILDREN.

IF PRODUCT IS SWALLOWED, GET MEDICAL HELP OR CONTACT A POISON CONTROL CENTER RIGHT AWAY.

DIRECTIONS

- APPLY LIBERALLY 15 MINUTES BEFORE SUN EXPOSURE. USE A WATER RESISTANT SUNSCREEN IF SWIMMING OR SWEATING. REAPPLY AT LEAST EVERY 2 HOURS.
- CHILDREN UNDER 6 MONTHS. ASK A DOCTOR. SUN PROTECTION MEASURES. SPENDING TIME IN THE SUN INCREASES YOUR RISK OF SKIN CANCER AND EARLY SKIN AGING. TO DECREASE THIS RISK, REGULARLY USE A SUNSCREEN WITH A BROAD SPECTRUM SPF OF 15 OR HIGHER AND OTHER SUN PROTECTION MEASURES INCLUDING:
- LIMIT TIME IN THE SUN, ESPECIALLY FROM 10 AM - 2 PM
- WEAR LONG-SLEEVE SHIRTS, PANTS, HATS, AND SUNGLASSES

CHILDREN UNDER 6 MONTHS: ASK A DOCTOR.

INACTIVE INGREDIENTS

AQUA (WATER), CAPRYLIC/CAPRIC TRIGLYCERIDE, CORN STARCH MODIFIED, CETEARYL OLIVATE, DIETHYLHEXYL 2,6-NAPHTHALATE, C12-15 ALKYL BENZOATE, SORBITAN OLIVATE, GLUCONOLACTONE, SQUALANE, GLYCERIN, CYCLOPENTASILOXANE, TOCOPHERYL ACETATE (D-ALPHA), GLYCINE SOJA (SOYBEAN) OIL, SODIUM HYALURONATE (L), XANTHAN GUM, CARBOMER, AMINOMETHYL PROPANOL, SODIUM BENZOATE, PHENETHYL ALCOHOL, CAPRYLYL CLYCOL, PHENOXYETHANOL, TRISODIUM ETHYLENEDIAMINE DISUCCINATE, POTASSIUM SORBATE. MADE IN USA.

OTHER INFORMATION

PROTECT THIS PRODUCT FROM EXCESSIVE HEAT AND DIRECT SUN.

QUESTIONS OR COMMENTS?

CALL TOLL FREE 1-800-792-5330